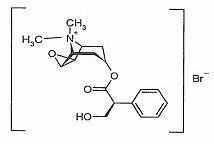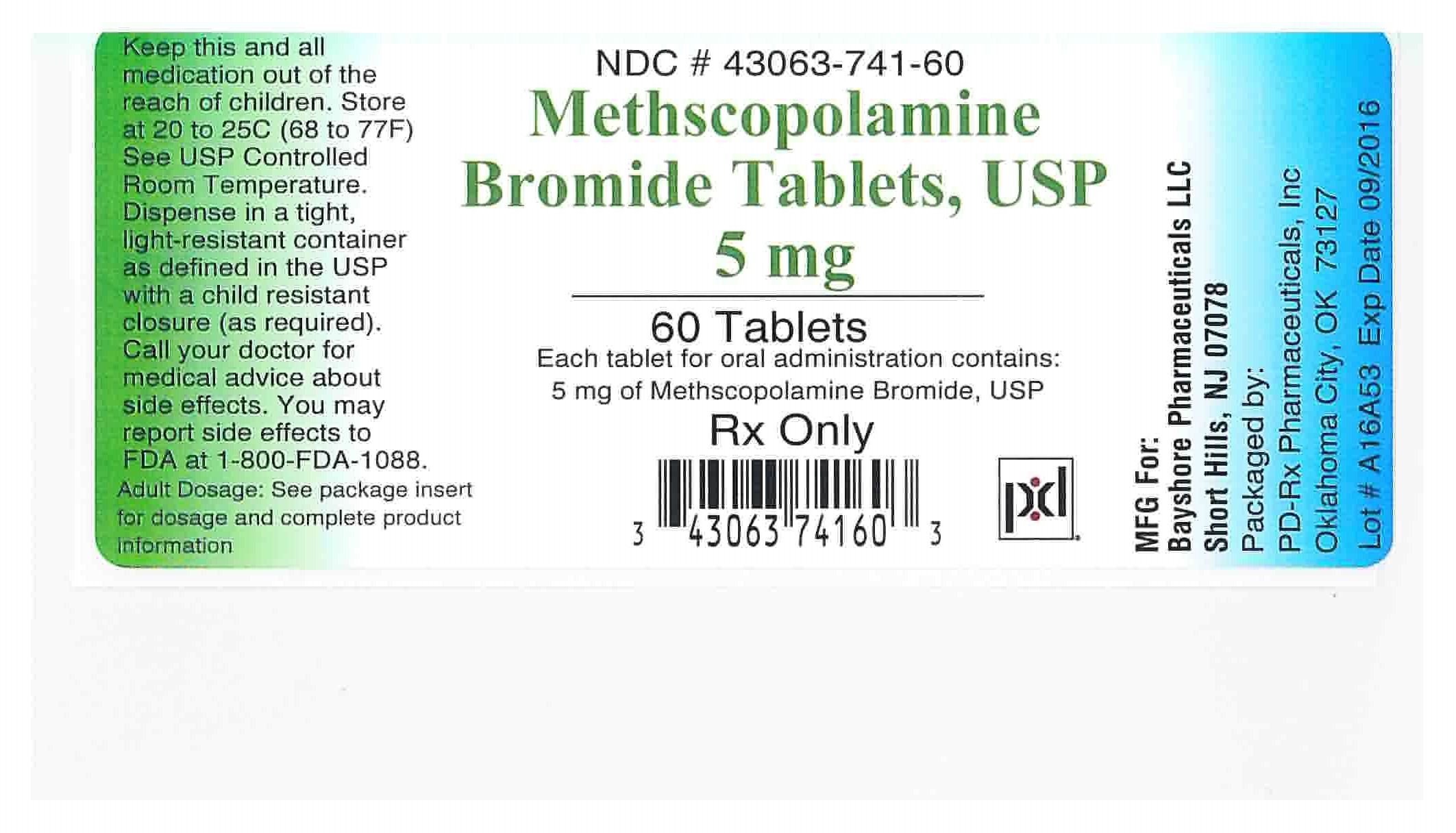 DRUG LABEL: METHSCOPOLAMINE BROMIDE
NDC: 43063-741 | Form: TABLET
Manufacturer: PD-Rx Pharmaceuticals, Inc.
Category: prescription | Type: HUMAN PRESCRIPTION DRUG LABEL
Date: 20260105

ACTIVE INGREDIENTS: METHSCOPOLAMINE BROMIDE 5 mg/1 1
INACTIVE INGREDIENTS: CELLULOSE, MICROCRYSTALLINE; STARCH, CORN; SILICON DIOXIDE; MAGNESIUM STEARATE

Methscopolamine Bromide Tablets, USP 5 mg
Rx Only

DESCRIPTION

Methscopolamine Bromide Tablets, USP 2.5 mg and 5 mg contain methscopolamine bromide USP, an anticholinergic, which occurs as white crystals, or as a white odorless crystalline powder. Methscopolamine bromide melts at about 225°C with decomposition. The drug is freely soluble in water, slightly soluble in alcohol, and insoluble in acetone and in chloroform.

The chemical name for methscopolamine bromide is 3-Oxa-9-azoniatricyclo [3.3.1.0^(2, 4)]nonane, 7-(3-hydroxy-1-oxo-2-phenylpropoxy)-9, 9-dimethyl-, bromide, [7(s)-(1α, 2β, 4β, 5α, 7β)]- and the molecular weight is 398.30.

The structural formula is represented below:

Methscopolamine Bromide Tablets, USP 2.5 mg for oral administration contain 2.5 mg of methscopolamine bromide USP. Methscopolamine Bromide Tablets, USP 5 mg for oral administration contain 5 mg of methscopolamine bromide USP.

Inactive ingredients: microcrystalline cellulose NF, pregelatinized starch NF, colloidal silicon dioxide NF, magnesium stearate NF.

Contains no lactose.

CLINICAL PHARMACOLOGY

Methscopolamine bromide is an anticholinergic agent which possesses most of the pharmacologic actions of that drug class. These include reduction in volume and total acid content of gastric secretion, inhibition of gastrointestinal motility, inhibition of salivary excretion, dilation of the pupil and inhibition of accommodation with resulting blurring of vision. Large doses may result in tachycardia.

PHARMACOKINETICS

Methscopolamine bromide is a quaternary ammonium derivative of scopolamine. As a class, these agents are poorly and unreliably absorbed.^(1, 2) Total absorption of quaternary ammonium derivatives of the alkaloids is 10 to 25%. Rate of absorption is not available. Quaternary ammonium salts have limited absorption from intact skin, and conjunctival penetration is poor.^1Little is known of the fate and excretion of most of these agents.^1Following oral administration, drug effects appear in about one hour and persist for 4 to 6 hours.^2Methscopolamine bromide has limited ability to cross the blood-brain barrier.^3,4,5The drug is excreted primarily in the urine and bile, or as unabsorbed drug in feces.^2There is no data on the presence of methscopolamine in breast milk; traces of atropine have been found after administration of atropine.^1

INDICATIONS AND USAGE

Adjunctive therapy for the treatment of peptic ulcer.

METHSCOPOLAMINE BROMIDE HAS NOT BEEN SHOWN TO BE EFFECTIVE IN CONTRIBUTING TO THE HEALING OF PEPTIC ULCER, DECREASING THE RATE OF RECURRENCE OR PREVENTING COMPLICATIONS.

CONTRAINDICATIONS

Glaucoma; obstructive uropathy (e.g., bladder neck obstruction due to prostatic hypertrophy); obstructive disease of the gastrointestinal tract (e.g., pyloroduodenal stenosis); paralytic ileus; intestinal atony of the elderly or debilitated patient; unstable cardiovascular status in acute hemorrhage; severe ulcerative colitis; toxic megacolon complicating ulcerative colitis; myasthenia gravis.

Methscopolamine Bromide Tablets, USP 2.5 mg and 5 mg is contraindicated in patients who are hypersensitive to methscopolamine bromide or related drugs.

WARNINGS

In the presence of high environmental temperature, heat prostration (fever and heat stroke due to decreased sweating) can occur with drug use.

Diarrhea may be an early symptom of incomplete intestinal obstruction, especially in patients with ileostomy or colostomy. In this instance treatment with this drug would be inappropriate and possibly harmful.

Methscopolamine bromide may produce drowsiness or blurred vision. The patient should be cautioned regarding activities requiring mental alertness such as operating a motor vehicle or other machinery or performing hazardous work while taking this drug.

With overdosage, a curare-like action may occur, i.e., neuromuscular blockade leading to muscular weakness and possible paralysis.

PRECAUTIONS

1. General precautions

Use Methscopolamine Bromide Tablets, USP 2.5 mg and 5 mg with caution in the elderly and in all patients with: autonomic neuropathy; hepatic or renal disease; or ulcerative colitis –large doses may suppress intestinal motility to the point of producing a paralytic ileus and for this reason precipitate or aggravate "toxic megacolon," a serious complication of the disease.

The drug also should be used with caution in patients having hyperthyroidism, coronary heart disease, congestive heart failure, tachyarrhythmia, tachycardia, hypertension, or prostatic hypertrophy.

2. Information for patient

See statement under WARNINGS.

3. Laboratory tests

Progress of the peptic ulcer under treatment should be followed by upper gastrointestinal contrast radiology or endoscopy to insure healing. Stool tests for occult blood and blood hemoglobin or hematocrit values should be followed to rule out bleeding from the ulcer.

4. Drug interactions

Additive anticholinergic effects may result from concomitant use with antipsychotics, tricyclic antidepressants, and other drugs with anticholinergic effects. Concomitant administration with antacids may interfere with the absorption of methscopolamine bromide.

5. Carcinogenesis, mutagenesis, impairment of fertility

No long-term studies in animals have been performed to evaluate carcinogenic potential.

6. Pregnancy

Teratogenic effects

Pregnancy Category C. Animal reproduction studies have not been conducted with methscopolamine bromide. It is also not known whether methscopolamine bromide can cause fetal harm when administered to a pregnant woman or can affect reproduction capacity. Methscopolamine bromide should be given to a pregnant woman only if clearly needed.

7. Nursing mothers

It is not known whether this drug is excreted in human milk. Because many drugs are excreted in human milk, caution should be exercised when methscopolamine bromide is administered to a nursing woman.

Anticholinergic drugs may suppress lactation.

8. Pediatric use

Safety and efficacy in children have not been established.

ADVERSE REACTIONS

The following adverse reactions have been observed, but there is not enough data to support an estimate of frequency.

Cardiovascular:Tachycardia, palpitation.

Allergic:Severe allergic reaction or drug idiosyncrasies including anaphylaxis.

CNS:Headaches, nervousness, mental confusion, drowsiness, dizziness.

Special Senses:Blurred vision, dilation of the pupil, cycloplegia, increased ocular tension, loss of taste.

Renal:Urinary hesitancy and retention.

Gastrointestinal:Nausea, vomiting, constipation, bloated feeling.

Dermatologic:Decreased sweating, urticaria and other dermal manifestations.

Miscellaneous:Xerostomia, weakness, insomnia, impotence, suppression of lactation.

DRUG ABUSE AND DEPENDENCE

Not applicable.

OVERDOSAGE

The symptoms of overdosage with Methscopolamine Bromide Tablets, USP 2.5 mg and 5 mg progress from intensification of the usual side effects to CNS disturbances (from restlessness and excitement to psychotic behavior), circulatory changes (flushing, fall in blood pressure, circulatory failure), respiratory failure, paralysis, and coma.

Measures to be taken are (1) induction of emesis and (2) injection of physostigmine 0.5 to 2 mg intravenously, and repeated as necessary up to a total of 5 mg. Fever may be treated symptomatically (alcohol sponging, ice packs). Excitement of a degree which demands attention may be managed with sodium thiopental 2% solution given slowly intravenously or chloral hydrate (100 to 200 mL of a 2% solution) by rectal infusion. In the event of progression of the curare-like effect to paralysis of the respiratory muscles, artificial respiration should be instituted and maintained until effective respiratory action returns.

The oral LD50in rats is 1,352 to 2,617 mg/kg.

No data is available on the dialyzability of methscopolamine bromide.

DOSAGE AND ADMINISTRATION

The average dosage of Methscopolamine Bromide Tablets, USP is 2.5 mg one-half hour before meals and 2.5 to 5 mg at bedtime. A starting dose of 12.5 mg daily will be clinically effective in most patients without the production of appreciable side effects.

If the patient is experiencing symptoms such as severe abdominal pain or cramping which demand prompt relief, the drug may be started on a daily dosage of 20 mg, administered in doses of 5 mg one-half hour before meals and at bedtime. If very unpleasant side effects develop promptly, the daily dosage should be reduced. If neither symptomatic relief nor side effects appear, the daily dosage may be increased. Some patients have tolerated 30 mg daily with no unpleasant reactions.

Patients whose dosage has been reduced to eliminate or modify side effects often continue to show adequate response both subjectively in relief of symptoms and objectively as measured by antisecretory effects.

The ultimate aim of therapy is to arrive at a dosage which provides maximal clinical effectiveness with a minimum of unpleasant side effects. Many patients report no side effects on a dosage which gives complete relief of symptoms. On the other hand, some patients have reported severe side effects without appreciable symptomatic relief. Such patients must be considered unsuited for this therapy. Usually they have been or will prove to be similarly intolerant to other anticholinergic drugs. If methscopolamine bromide is to be used in a patient who gives a history of such intolerance, it should be started at a low dosage.

HOW SUPPLIED

Methscopolamine Bromide Tablets, USP 5 mg are available as white, oval tablets, debossed with "BY2" on one side and plain on the other side, in the following package size:

Bottles of 60 (NDC 43063-741-60)

Store at 20° to 25°C (68° to 77°F) [see USP Controlled Room Temperature]. Dispense in a tight, light-resistant container as defined in the USP, with a child-resistant closure (as required).

KEEP THIS AND ALL MEDICATIONS OUT OF THE REACH OF CHILDREN.

REFERENCES

1. Gilman A, Gilman AB, Goodman LA, eds.

The Pharmacological Basis of Therapeutics.6th ed. New York: MacMillan Publishing Company.1980.

2. American Hospital Formulary Service. American Society of Hospital Pharmacists. Bethesda, Maryland.

3. Domino EF, Corasen G. Central and Peripheral Effects of Muscarinic Cholinergic Blocking Agents in Man. Anesthesiology1967;28:568-574.

4. Mogensen L, Orinius E. Arrhythmic Complications after Parasympathetic Treatment of Bradyarrhythmias in a Coronary Care Unit. Acta Med Scand1971;190:495-498.

5. Neeld JB Jr., et al. Cardiac Rate and Rhythm Changes with Atropine and Methscopolamine. Clin Pharmacol Ther1975;17(3):290-295.

Rx Only

Call your doctor for medical advice about side effects. You may report side effects to FDA at 1-800-FDA-1088 or Unichem Pharmaceuticals (USA) Inc. at 1-866-562-4616

MADE IN USA

Distributed by:

UNICHEM PHARMACEUTICALS (USA), INC.

East Brunswick, NJ 08816 USA

Rev. 10/2025

400036